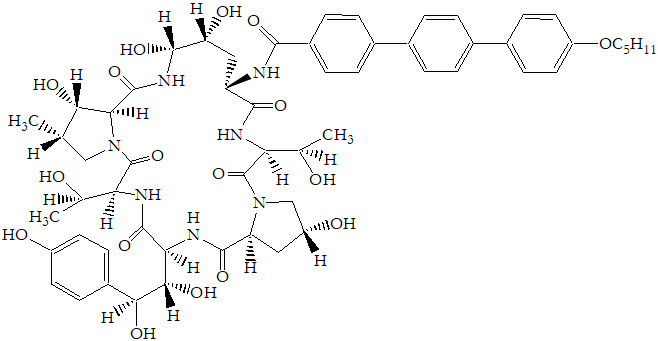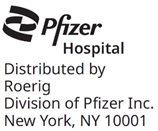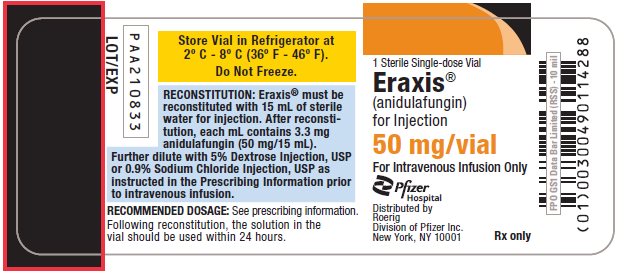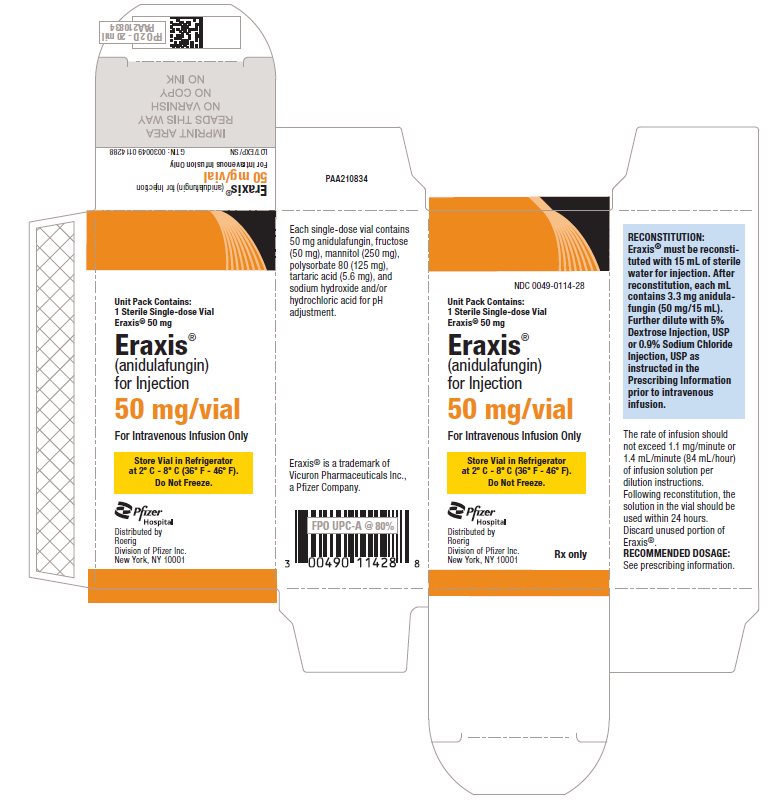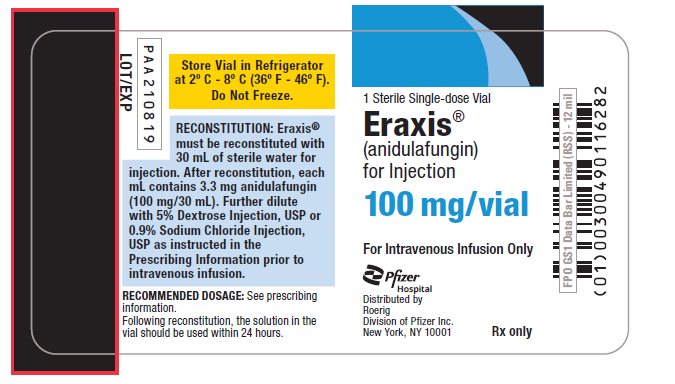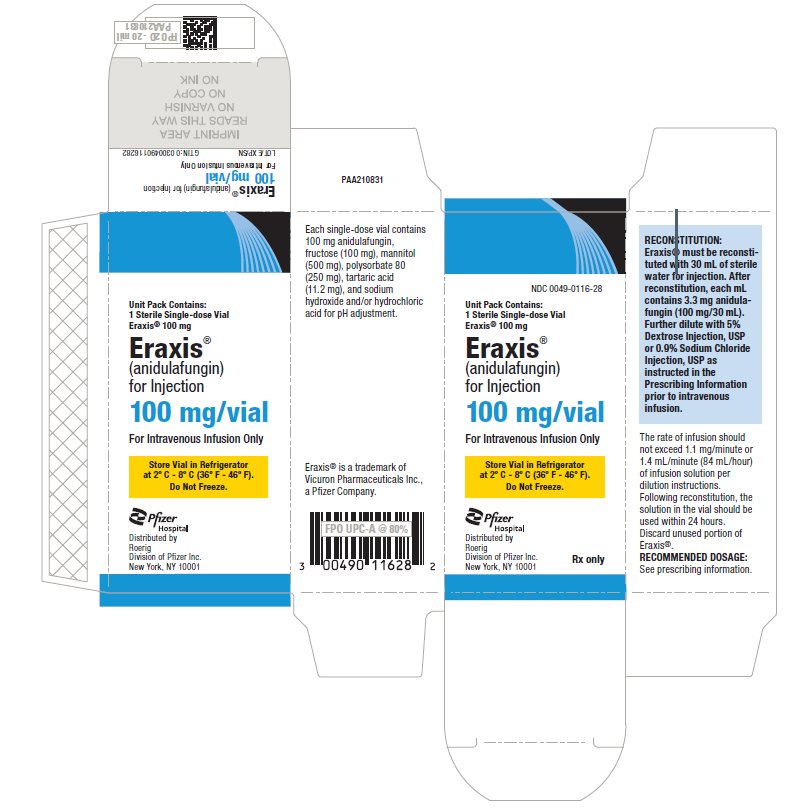 DRUG LABEL: ERAXIS
NDC: 0049-0114 | Form: INJECTION, POWDER, LYOPHILIZED, FOR SOLUTION
Manufacturer: Roerig
Category: prescription | Type: HUMAN PRESCRIPTION DRUG LABEL
Date: 20250819

ACTIVE INGREDIENTS: ANIDULAFUNGIN 50 mg/15 mL
INACTIVE INGREDIENTS: FRUCTOSE 50 mg/15 mL; MANNITOL 250 mg/15 mL; POLYSORBATE 80 125 mg/15 mL; TARTARIC ACID 5.6 mg/15 mL; SODIUM HYDROXIDE; HYDROCHLORIC ACID

HIGHLIGHTS OF PRESCRIBING INFORMATION

These highlights do not include all the information needed to use ERAXIS safely and effectively. See full prescribing information for ERAXIS.
ERAXIS® (anidulafungin) for injection, for intravenous use
Initial U.S. Approval: 2006

1 INDICATIONS AND USAGE

ERAXIS is an echinocandin antifungal indicated for the treatment of the following infections:

- Candidemia and other forms of Candida infections (intra-abdominal abscess and peritonitis) in adults and pediatric patients (1 month of age and older) (1.1)
- Esophageal candidiasis in adults (1.2)

Limitations of use

- ERAXIS has not been studied in adult and pediatric patients with endocarditis, osteomyelitis, and meningitis due to Candida or in sufficient numbers of neutropenic patients. The dosage of ERAXIS for the treatment of Candida dissemination into the CNS and the eye has not been established. (1.3, 5.3, 8.4)
- ERAXIS is associated with high relapse rates in esophageal candidiasis. (1.3, 14.2)

2 DOSAGE AND ADMINISTRATION

Adults | Pediatric Patients 1 Month of Age and Older
Candidemia and other forms of Candida infections
200 mg loading dose on Day 1, followed by 100 mg once daily maintenance dose thereafter for at least 14 days after the last positive culture (2.1) | 3 mg/kg (not to exceed 200 mg) loading dose on Day 1, followed by 1.5 mg/kg (not to exceed 100 mg) once daily maintenance dose thereafter for at least 14 days after the last positive culture (2.2)
Esophageal candidiasis
100 mg loading dose on Day 1, followed by 50 mg once daily maintenance dose thereafter for a minimum of 14 days and for at least 7 days following resolution of symptoms (2.1) | Not Approved

Rate of Infusion for Adults and Pediatric Patients

The rate of infusion should not exceed 1.1 mg/minute [equivalent to 1.4 mL/minute or 84 mL/hour when reconstituted and diluted per instructions] (2.3, 2.4)

3 DOSAGE FORMS AND STRENGTHS

For injection: 50 mg, and 100 mg as a lyophilized powder in a single-dose vial for reconstitution (3)

4 CONTRAINDICATIONS

- Known hypersensitivity to anidulafungin, any component of ERAXIS, or other echinocandins (4, 5.2)
- Known or suspected Hereditary Fructose Intolerance (HFI) (4, 5.4)

5 WARNINGS AND PRECAUTIONS

- Hepatic Effects: Risk of abnormal liver tests, hepatitis, hepatic failure; monitor hepatic function during therapy. (5.1, 13.2)
- Hypersensitivity: Anaphylaxis, including shock has been reported. Risk of infusion-related adverse reactions, possibly histamine-mediated, including rash, urticaria, flushing, pruritus, bronchospasm, dyspnea, and hypotension; to reduce occurrence, do not exceed a rate of infusion of 1.1 mg/minute. (2.4, 5.2)
- Risk of Neonatal Toxicity Associated with Polysorbates: ERAXIS contains polysorbate 80, an inactive ingredient. Thrombocytopenia, renal dysfunction, hepatomegaly, cholestasis, ascites, hypotension and metabolic acidosis haves been reported in low-birth weight infants receiving high doses of polysorbate. ERAXIS is not approved in pediatric patients younger than 1 month of age. (5.3, 8.4)
- Hereditary Fructose Intolerance (HFI): ERAXIS contains fructose. Risk of metabolic crisis with life-threatening hypoglycemia, hypophosphatemia, lactic acidosis, and hepatic failure. Obtain history of HFI symptoms in pediatric patients before ERAXIS administration. (5.4, 8.4)

6 ADVERSE REACTIONS

Adults

- Candidemia and other forms of Candida infections: Most common adverse reactions (≥15%) are hypokalemia, nausea, diarrhea, vomiting, pyrexia, insomnia, hypotension. (6.1)
- Esophageal candidiasis: Most common adverse reactions (≥5%) are diarrhea, pyrexia, anemia, headache, vomiting, nausea, dyspepsia, oral candidiasis, and hypokalemia. (6.1)

Pediatric Patients (1 month and older)

Candidemia and other forms of Candida infections: Most common adverse reactions (≥ 5%): diarrhea, vomiting, pyrexia, abdominal pain, anemia, thrombocytopenia, alanine aminotransferase (ALT) and aspartate aminotransferase (AST) increased, hypoglycemia, epistaxis, and rash. (6.1)
To report SUSPECTED ADVERSE REACTIONS, contact Pfizer Inc at 1-800-438-1985 or FDA at 1-800-FDA-1088 or www.fda.gov/medwatch.

8 USE IN SPECIFIC POPULATIONS

- Pregnancy: Based on findings from animal studies, ERAXIS can cause fetal harm when administered to a pregnant woman. Inform pregnant woman of the risk to the fetus. (8.1)
- Pediatric Use: The safety and effectiveness in patients younger than 1 month of age has not been established. (8.4)

FULL PRESCRIBING INFORMATION

1 INDICATIONS AND USAGE

1.1 Candidemia and Other Forms of Candida Infections (Intra-abdominal Abscess and Peritonitis)

ERAXIS is indicated for the treatment of candidemia and the following Candida infections: intra-abdominal abscess and peritonitis in adults and pediatric patients 1 month of age and older [see Clinical Studies (14.1) and Microbiology (12.4)].

1.2 Esophageal Candidiasis

ERAXIS is indicated for the treatment of esophageal candidiasis in adults [see Indications and Usage (1.3), Clinical Studies (14.2)].

1.3 Limitations of Use

- ERAXIS has not been studied in adult and pediatric patients with endocarditis, osteomyelitis, and meningitis due to Candida, and has not been studied in sufficient numbers of neutropenic patients to determine efficacy in this group. The dosage of ERAXIS for the treatment of Candida dissemination into the CNS and the eye has not been established [see Warning and Precautions (5.3), Use in Specific Populations (8.4)].
- ERAXIS is associated with high relapse rates in esophageal candidiasis [see Clinical Studies (14.2)].

1.4 Usage

Specimens for fungal culture and other relevant laboratory studies (including histopathology) should be obtained prior to therapy to isolate and identify causative organism(s). Therapy may be instituted before the results of the cultures and other laboratory studies are known. However, once these results become available, antifungal therapy should be adjusted accordingly.

2 DOSAGE AND ADMINISTRATION

2.1 Recommended Dosage in Adults

Candidemia and other Candida infections (intra-abdominal abscess and peritonitis)

The recommended dose is a single 200 mg loading dose of ERAXIS on Day 1, followed by a 100 mg once daily maintenance dose thereafter. Duration of treatment should be based on the patient's clinical response. In general, antifungal therapy should continue for at least 14 days after the last positive culture.

Esophageal Candidiasis

The recommended dose is a single 100 mg loading dose of ERAXIS on Day 1, followed by a 50 mg once daily maintenance dose thereafter. Patients should be treated for a minimum of 14 days and for at least 7 days following resolution of symptoms. Duration of treatment should be based on the patient's clinical response. Because of the risk of relapse of esophageal candidiasis in patients with HIV infection, suppressive antifungal therapy may be considered after a course of treatment.

2.2 Recommended Dosage in Pediatric Patients (1 Month of Age and Older)

Candidemia and other Candida infections (intra-abdominal abscess and peritonitis)

The recommended dose is a single loading dose of 3 mg/kg (not to exceed 200 mg) of ERAXIS on Day 1, followed by a once daily maintenance dose of 1.5 mg/kg (not to exceed 100 mg) of ERAXIS thereafter. Overall antifungal treatment should continue for at least 14 days after the last positive culture.

2.3 Preparation for Administration

ERAXIS for Injection must be reconstituted with sterile Water for Injection and subsequently diluted only with 5% Dextrose Injection, USP or 0.9% Sodium Chloride Injection, USP (normal saline), prior to administration.

The compatibility of reconstituted ERAXIS with intravenous substances, additives, or medications other than 5% Dextrose Injection, USP or 0.9% Sodium Chloride Injection, USP (normal saline) has not been established. Do NOT dilute with other solutions or co-infuse with other medications or electrolytes. The infusion solution must not be frozen.

Reconstitution of the 50 mg/vial

Aseptically reconstitute each 50 mg vial with 15 mL of sterile Water for Injection to provide a concentration of 3.33 mg/mL.

Reconstitution of the 100 mg/vial

Aseptically reconstitute each 100 mg vial with 30 mL of sterile Water for Injection to provide a concentration of 3.33 mg/mL.

Storage of the Reconstituted Solution

ERAXIS reconstituted solution can be stored at 25°C (77°F) for up to 24 hours prior to dilution into the infusion solution. Chemical and physical in-use stability of the reconstituted solution has been demonstrated for 24 hours at 25°C (77°F). From a microbiological point of view, following good aseptic practices, the reconstituted solution can be utilized for up to 24 hours when stored at 25°C.

2.4 Dilution and Administration of the Infusion

Parenteral drug products should be inspected visually for particulate matter and discoloration prior to administration, whenever solution and container permit. If particulate matter or discoloration is identified, discard the solution.

Adult Patients

Aseptically transfer the contents of the reconstituted vial(s) into the appropriately sized IV bag (or bottle) containing either 5% Dextrose Injection, USP or 0.9% Sodium Chloride Injection, USP (normal saline). See Table 1 for the dilution to a concentration of 0.77 mg/mL for the final infusion solution and infusion instructions for each dose. The rate of infusion should not exceed 1.1 mg/minute (equivalent to 1.4 mL/minute or 84 mL/hour when reconstituted and diluted per instructions) [see Warnings and Precautions (5.2)].

Table 1: Dilution Requirements for ERAXIS Administration
Dose | Number of Vials Required | Total Reconstituted Volume Required | Infusion Volume [Either 5% Dextrose Injection, USP or 0.9% Sodium Chloride Injection, USP (normal saline)] | Total Infusion Volume [Infusion solution concentration is 0.77 mg/mL] | Rate of Infusion | Minimum Duration of Infusion
50 mg | 1–50 mg | 15 mL | 50 mL | 65 mL | 1.4 mL/min or 84 mL/ hour | 45 min
100 mg | 2–50 mg or 1–100 mg | 30 mL | 100 mL | 130 mL | 1.4 mL/min or 84 mL/ hour | 90 min
200 mg | 4–50 mg or 2–100 mg | 60 mL | 200 mL | 260 mL | 1.4 mL/min or 84 mL/ hour | 180 min

Pediatric Patients

The volume of infusion solution required to deliver the dose is dependent on the weight of the child. The reconstituted solution must be further diluted to a concentration of 0.77 mg/mL for the final infusion solution. A programmable syringe or infusion pump is recommended. The rate of infusion should not exceed 1.1 mg/minute (equivalent to 1.4 mL/minute or 84 mL/hour when reconstituted and diluted per instructions) [see Warnings and Precautions (5.2)].

Steps for the Preparation of Pediatric Doses below 50 mg

1. Calculate pediatric patient dose and aseptically reconstitute vial(s) required according to reconstitution instructions to provide a concentration of 3.33 mg/mL (if dose is 50 mg or above, see preparation instructions for Adult Patients above) [see Dosage and Administration (2.2, 2.3)].
2. Calculate the volume (mL) of reconstituted ERAXIS required:
  [Volume of reconstituted ERAXIS (mL) = Dose of ERAXIS (mg) ÷ 3.33 mg/mL]
3. Calculate the total volume of the infusion solution (mL) that contains a final concentration of 0.77 mg/mL:
  [Total volume of infusion solution (mL) = Dose of ERAXIS (mg) ÷ 0.77 mg/mL]
4. Calculate the volume of diluent [5% Dextrose Injection, USP or 0.9% Sodium Chloride Injection, USP (normal saline)] required to prepare the infusion solution: [Volume of diluent (mL) = Total volume of final infusion solution (mL) – Volume of reconstituted ERAXIS (mL)]
5. Prepare the infusion solution by aseptically transferring the required volumes (mL) of the reconstituted ERAXIS and diluent [5% Dextrose Injection, USP or 0.9% Sodium Chloride Injection, USP (normal saline)] into an infusion syringe or IV infusion bag needed for administration.

Storage of the Infusion Solution

ERAXIS infusion solution can be stored at temperatures up to 25°C (77°F) for up to 48 hours. Do not freeze. Chemical and physical in-use stability of the infusion solution has been demonstrated for 48 hours at 25°C (77°F). From a microbiological point of view, following good aseptic practices, the infusion solution can be utilized for up to 48 hours from preparation when stored at 25°C.

3 DOSAGE FORMS AND STRENGTHS

For injection: 50 mg, and 100 mg of anidulafungin as a white to off-white sterile lyophilized powder in a single-dose vial for reconstitution.

4 CONTRAINDICATIONS

ERAXIS is contraindicated in:

- Patients with known hypersensitivity to anidulafungin, any component of ERAXIS, or other echinocandins [see Warnings and Precautions (5.2)]
- Patients with known or suspected Hereditary Fructose Intolerance (HFI) [see Warnings and Precautions (5.4)]

5 WARNINGS AND PRECAUTIONS

5.1 Hepatic Adverse Reactions

Laboratory abnormalities in liver tests have been seen in healthy volunteers and pediatric patients treated with ERAXIS. In some patients with serious underlying medical conditions who were receiving multiple concomitant medications along with ERAXIS, clinically significant hepatic abnormalities have occurred. Isolated cases of significant hepatic dysfunction, hepatitis, or hepatic failure have been reported in patients; a causal relationship to ERAXIS has not been established [see Adverse Reactions (6.1) and Nonclinical Toxicology (13.2)]. Patients who develop abnormal liver tests during ERAXIS therapy should be monitored for evidence of worsening hepatic tests and evaluated for risk/benefit of continuing ERAXIS therapy.

5.2 Anaphylactic and Hypersensitivity Reactions

Anaphylactic reactions, including shock were reported with the use of ERAXIS. If these reactions occur, ERAXIS should be discontinued and appropriate treatment administered [see Adverse Reactions (6)].

Infusion-related adverse reactions, possibly histamine-mediated, have been reported with ERAXIS, including rash, urticaria, flushing, pruritus, bronchospasm, dyspnea, and hypotension [see Adverse Reactions (6)]. To reduce occurrence of these reactions, do not exceed a rate of ERAXIS infusion of 1.1 mg/minute [see Dosage and Administration (2.4)].

5.3 Risk of Neonatal Toxicity Associated with Polysorbates

ERAXIS contains polysorbate 80, an inactive ingredient. Thrombocytopenia, renal dysfunction, hepatomegaly, cholestasis, ascites, hypotension, and metabolic acidosis have been reported in low-birth weight infants receiving high doses of polysorbate. Polysorbate toxicity has not been reported with ERAXIS. ERAXIS is not approved in pediatric patients younger than 1 month of age [see Indications and Usage (1.1, 1.3), Use in Specific Populations (8.4)].

5.4 Risk in Patients with Hereditary Fructose Intolerance (HFI)

ERAXIS contains fructose, an inactive ingredient, and may precipitate a metabolic crisis that may include, but is not limited to life-threatening hypoglycemia, hypophosphatemia, lactic acidosis, and hepatic failure in patients with HFI. Obtain careful history of HFI symptoms (nausea, vomiting, abdominal pain) with fructose/sucrose exposure prior to ERAXIS administration because a diagnosis of HFI may not yet be established in pediatric patients [see Contraindications (4) and Use in Specific Populations (8.4)].

6 ADVERSE REACTIONS

The following most serious adverse reactions are described elsewhere in other labeling sections:

- Hepatic Adverse Reactions [see Warnings and Precautions (5.1)]
- Anaphylactic and Hypersensitivity Reactions [see Warnings and Precautions (5.2)]

6.1 Clinical Trials Experience

Because clinical trials are conducted under widely varying conditions, adverse reaction rates observed in the clinical trials of a drug cannot be directly compared to rates in the clinical trials of another drug and may not reflect the rates observed in practice.

Clinical Trials Experience in Adults

The safety of ERAXIS for Injection was assessed in 929 individuals, including 257 healthy subjects and 672 patients in clinical trials of candidemia, other forms of Candida infections, and esophageal candidiasis. A total of 633 patients received ERAXIS at daily doses of either 50 mg or 100 mg. A total of 481 patients received ERAXIS for ≥14 days.

Candidemia/other Candida Infections

Three trials (one comparative vs. fluconazole, two non-comparative) assessed the efficacy and safety of ERAXIS (100 mg) in patients with candidemia and other Candida infections.

The data described below reflect exposure to ERAXIS and fluconazole in 127 and 118 patients, respectively, with candidemia and other forms of invasive candidiasis, in the randomized, comparative trial of the efficacy and safety of ERAXIS to that of fluconazole. In ERAXIS-treated patients, the age range was 16–89 years, the gender distribution was 51% male and 49% female, and the race distribution was 72% White, 18% Black/African American, 9% other races. Patients were randomized to receive once daily IV ERAXIS (200 mg loading dose followed by 100 mg maintenance dose) or IV fluconazole (800 mg loading dose followed by 400 mg maintenance dose). Treatment was administered for at least 14 and not more than 42 days.

The number of patients with adverse reactions leading to discontinuation of study medication was 11.5% in the ERAXIS arm and 21.6% in the fluconazole arm. The most common adverse reactions leading to study drug discontinuation were multi-organ failure (2.3%) and systemic Candida infection (1.5%) in the ERAXIS arm.

Table 2 presents adverse reactions that were reported in ≥5% of subjects receiving ERAXIS or fluconazole therapy in this trial.

Table 2: Adverse Reactions Reported in ≥5% of Adult Patients Receiving ERAXIS or Fluconazole Therapy for Candidemia/other Candida Infections [A patient who experienced multiple reactions within a Body System or preferred term was counted one time for that class, one time for the preferred term and one time for "subjects with at least one adverse reaction".] , [This trial was not designed to support comparative claims for ERAXIS for the adverse reactions reported in this table.]
Adverse Reaction | ERAXIS 100 mg N=131 | Fluconazole 400 mg N=125
 | N (%) | N (%)
Subjects with a least one adverse reaction | 130 (99) | 122 (98)
Gastrointestinal disorders | 81 (62) | 72 (58)
Nausea | 32 (24) | 15 (12)
Diarrhea | 24 (18) | 23 (18)
Vomiting | 23 (18) | 12 (10)
Constipation | 11 (8) | 14 (11)
Abdominal pain | 8 (6) | 16 (13)
General disorders and administration site conditions | 70 (53) | 76 (61)
Pyrexia | 23 (18) | 23 (18)
Edema peripheral | 14 (11) | 16 (13)
Chest pain | 7 (5) | 6 (5)
Respiratory, thoracic, and mediastinal disorders | 67 (51) | 55 (44)
Dyspnea | 15 (12) | 4 (3)
Pleural effusion | 13 (10) | 11 (9)
Cough | 9 (7) | 7 (6)
Respiratory distress | 8 (6) | 2 (2)
Investigations | 66 (50) | 46 (37)
Blood alkaline phosphatase increased | 15 (12) | 14 (11)
White blood cell increased | 11 (8) | 3 (2)
Hepatic enzyme increased | 7 (5) | 14 (11)
Blood creatinine increased | 7 (5) | 1 (1)
Metabolism and nutrition disorders | 61 (47) | 61 (49)
Hypokalemia | 33 (25) | 24 (19)
Hypomagnesemia | 15 (12) | 14 (11)
Hypoglycemia | 9 (7) | 10 (8)
Hyperkalemia | 8 (6) | 14 (11)
Hyperglycemia | 8 (6) | 8 (6)
Dehydration | 8 (6) | 2 (2)
Vascular disorders | 50 (38) | 41 (33)
Hypotension | 19 (15) | 18 (14)
Hypertension | 15 (12) | 5 (4)
Deep vein thrombosis | 13 (10) | 9 (7)
Psychiatric disorders | 48 (37) | 45 (36)
Insomnia | 20 (15) | 12 (10)
Confusional state | 10 (8) | 10 (8)
Depression | 8 (6) | 5 (4)
Blood and lymphatic system disorders | 34 (26) | 36 (29)
Anemia | 12 (9) | 20 (16)
Thrombocythemia | 8 (6) | 1 (1)
Leukocytosis | 7 (5) | 6 (5)
Skin and subcutaneous tissue disorders | 30 (23) | 32 (26)
Decubitus ulcer | 7 (5) | 10 (8)
Nervous system disorders | 27 (21) | 31 (25)
Headache | 11 (8) | 10 (8)
Musculoskeletal and connective tissue disorders | 27 (21) | 25 (20)
Back pain | 7 (5) | 13 (10)

Esophageal Candidiasis

The data described below reflect exposure to ERAXIS and fluconazole in 300 and 301 patients, respectively, with esophageal candidiasis in a randomized trial comparing the efficacy and safety of ERAXIS to that of oral fluconazole. In ERAXIS-treated patients, the age range was 18–68 years, the gender distribution was 42% male and 58% female and the race distribution was 15% White, 49% Black/African American, 15% Asian, 0.3 % Hispanic, 21% other races. Patients were randomized to receive IV ERAXIS (100 mg on day 1, followed by 50 mg per day) or oral fluconazole (200 mg on day 1, followed by 100 mg per day) for 7 days beyond resolution of symptoms (range, 14–21 days).

Twenty-eight (9%) patients in the ERAXIS arm and 36 (12%) patients in the fluconazole arm had adverse reactions related to study medication. The most common adverse reactions leading to study discontinuation were maculopapular rash (1 patient) for the ERAXIS arm. The most common adverse reactions leading to discontinuation were rash (1 patient) and increased AST (1 patient) for the fluconazole arm.

Table 3 presents adverse reactions that were reported in ≥5% of subjects receiving ERAXIS therapy.

Table 3: Adverse Reactions Reported in ≥5% of Adult Patients Receiving ERAXIS or Fluconazole Therapy for Esophageal Candidiasis [A patient who experienced multiple reactions within a Body System or preferred term was counted one time for that class, one time for the preferred term and one time for "subjects with at least one adverse reaction".] , [This trial was not designed to support comparative claims for ERAXIS for the adverse reactions reported in this table.]
Adverse Reaction | ERAXIS 50 mg N=300 | Fluconazole 100 mg N=301
 | N (%) | N (%)
Subjects with a least one adverse reaction | 239 (80) | 227 (75)
Infections and infestations | 115 (38) | 99 (33)
Oral candidiasis | 15 (5) | 10 (3)
Gastrointestinal disorders | 106 (35) | 113 (38)
Diarrhea | 27 (9) | 26 (9)
Vomiting | 27 (7) | 30 (10)
Nausea | 20 (7) | 23 (8)
Dyspepsia | 20 (7) | 21 (7)
Blood and lymphatic system disorders | 55 (18) | 50 (17)
Anemia | 25 (8) | 22 (7)
Metabolism and nutrition disorders | 50 (17) | 46 (15)
Hypokalemia | 14 (5) | 17 (6)
General disorders and administration site condition | 49 (16) | 54 (18)
Pyrexia | 27 (9) | 28 (9)
Nervous system disorders | 39 (13) | 36 (12)
Headache | 25 (8) | 20 (7)

Less Common Adverse Reactions in Adult Patients with Candidemia/other Candida Infections and Esophageal Candidiasis

The following selected adverse reactions occurred in <2% of patients:

Blood and Lymphatic: coagulopathy, thrombocytopenia

Cardiac: atrial fibrillation, bundle branch block (right), sinus arrhythmia, ventricular extrasystoles

Eye: eye pain, vision blurred, visual disturbance

General and Administration Site: infusion related reaction, peripheral edema, rigors

Hepatobiliary: abnormal liver function tests, cholestasis, hepatic necrosis

Infections: clostridial infection

Investigations: amylase increased, bilirubin increased, CPK increased, electrocardiogram QT prolonged, gamma-glutamyl transferase increased, lipase increased, potassium decreased, prothrombin time prolonged, urea increased

Nervous System: convulsion, dizziness

Respiratory, Thoracic and Mediastinal: cough

Skin and Subcutaneous Tissue: angioneurotic edema, erythema, pruritus, sweating increased, urticaria

Vascular: flushing, hot flushes, thrombophlebitis superficial

Clinical Trials Experience in Pediatric Patients with Candidemia/Invasive Candidiasis

The safety of ERAXIS was investigated in 68 pediatric patients from 1 month to less than 18 years of age with candidemia/invasive candidiasis in a prospective, open-label, non-comparative pediatric trial [see Clinical Studies (14.1)]. Overall, the safety profile of ERAXIS in the pediatric patients 1 month and older was similar to that of adults.

Most Common Adverse Reactions

The most common adverse reactions occurring in ≥5% of pediatric patients receiving ERAXIS therapy in the clinical trial are displayed by body system in Table 4.

Table 4 Adverse Reactions Occurring in ≥5% of Pediatric Patients Receiving ERAXIS Therapy for Candidemia/other Candida Infections [Reflects adverse reactions including those that started on or after first dose of anidulafungin through 6-week follow-up for patients who did not receive oral fluconazole, and those that started between first dose and last dose of anidulafungin for patients who received oral fluconazole.] , [A patient who experienced multiple reactions within a Body System or preferred term was counted one time for that class, one time for the preferred term and one time for "subjects with at least one adverse reaction".]
Adverse Reaction | 1 month to <2 years N=19 | 2 to <5 years N=19 | 5 to <18 years N=30 | Overall N=68
 | n (%) | n (%) | n (%) | n (%)
Subjects with a least one adverse reaction | 17 (90) | 14 (74) | 24 (80) | 55 (81)
Blood and lymphatic system disorders | 9 (47) | 3 (16) | 4 (13) | 16 (24)
Anemia | 5 (26) | 2 (11) | 0 | 7 (10)
Thrombocytopenia | 2 (11) | 1 (5) | 1 (3) | 4 (6)
Gastrointestinal disorders | 8 (42) | 8 (42) | 12 (40) | 28 (41)
Diarrhea | 4 (21) | 2 (11) | 5 (17) | 11 (16)
Vomiting | 4 (21) | 5 (26) | 2 (7) | 11 (16)
Abdominal pain [Includes such terms as: abdominal pain and abdominal pain upper.] | 0 | 4 (21) | 2 (7) | 6 (9)
General disorders and administration site condition | 5 (26) | 6 (32) | 9 (30) | 20 (29)
Pyrexia | 4 (21) | 3 (16) | 5 (17) | 12 (18)
Laboratory Investigations | 4 (21) | 4 (21) | 8 (27) | 16 (24)
Alanine aminotransferase increased | 2 (11) | 2 (11) | 2 (7) | 6 (9)
Aspartate aminotransferase increased | 2 (11) | 1 (5) | 1 (3) | 4 (6)
Metabolism and nutrition disorders | 3 (16) | 4 (21) | 6 (20) | 13 (19)
Hypoglycemia | 1 (5) | 2 (11) | 1 (3) | 4 (6)
Respiratory, thoracic and mediastinal disorders | 5 (26) | 5 (26) | 5 (17) | 15 (22)
Epistaxis | 1 (5) | 2 (11) | 3 (10) | 6 (9)
Skin and subcutaneous tissue disorders | 6 (32) | 5 (26) | 5 (17) | 16 (24)
Rash [Includes such terms as: rash and rash generalized.] | 3 (16) | 1 (5) | 2 (7) | 6 (9)

Other adverse reactions were reported in 2 or more pediatric patients and in less than 5% of the 68 pediatric patients treated with ERAXIS in the clinical trial:

Blood and Lymphatic System Disorders: pancytopenia, thrombocytosis, febrile neutropenia, leukopenia, neutropenia

Eye Disorders: Periorbital edema

Gastrointestinal Disorders: gastroesophageal reflux disease, abdominal distension, nausea, stomatitis, dry mouth

General Disorders and Administrative Site Conditions: chest pain, edema peripheral

Infections and Infestations: bacteremia, device related infection, gastroenteritis, lower respiratory tract infection, upper respiratory tract infection, urinary tract infection

Laboratory Investigations: gamma-glutamyltransferase increased, transaminases increased

Metabolism and Nutrition Disorders: hypocalcemia, hypokalemia, hyponatremia, hypoproteinemia

Musculoskeletal and Connective Tissue Disorders: back pain, pain in extremity

Nervous System Disorders: headache, tremor, seizure

Psychiatric Disorders: agitation

Respiratory, Thoracic and Mediastinal Disorders: hemoptysis

Vascular Disorders: hypotension

6.2 Post-marketing Experience

The following adverse reactions have been identified during post approval use of anidulafungin. Because these reactions are reported voluntarily from a population of uncertain size, it is not always possible to reliably estimate their frequency or establish a causal relationship to drug exposure.

Immune: Anaphylactic shock, anaphylactic reaction, bronchospasm [see Warnings and Precautions (5.2)].

7 DRUG INTERACTIONS

7.1 Cyclosporine

Administration of multiple doses of anidulafungin and cyclosporine to healthy subjects resulted in no significant alteration in the steady state pharmacokinetics of either drug. No dosage adjustment of cyclosporine or anidulafungin is needed when the two drugs are co-administered [see Clinical Pharmacology (12.3)].

7.2 Voriconazole

Administration of multiple doses of anidulafungin and voriconazole to healthy subjects resulted in no significant alteration in the steady state pharmacokinetics of either drug. No dosage adjustment of voriconazole or anidulafungin is needed when the two drugs are co-administered [see Clinical Pharmacology (12.3)].

7.3 Tacrolimus

Administration of multiple doses of anidulafungin and a single-dose of tacrolimus to healthy subjects resulted in no significant alteration in the steady state pharmacokinetics of either drug. No dosage adjustment of tacrolimus or anidulafungin is needed when the two drugs are co-administered [see Clinical Pharmacology (12.3)].

7.4 Rifampin

Administration of multiple doses of anidulafungin and rifampin to patients resulted in no significant alteration in the steady state pharmacokinetics of anidulafungin. No dosage adjustment of anidulafungin is needed when it is co-administered with rifampin [see Clinical Pharmacology (12.3)].

7.5 Amphotericin B Liposome for Injection

Administration of multiple doses of anidulafungin and liposomal amphotericin B to patients resulted in no significant alteration in the steady state pharmacokinetics of anidulafungin. No dosage adjustment of anidulafungin is needed when it is co-administered with liposomal amphotericin B [see Clinical Pharmacology (12.3)].

8 USE IN SPECIFIC POPULATIONS

8.1 Pregnancy

Risk Summary

Based on findings from animal studies, ERAXIS can cause fetal harm when administered to a pregnant woman. There are no available human data on the use of ERAXIS in pregnant women to inform a drug-associated risk of adverse developmental outcomes. In animal reproduction studies fetal toxicity was observed in the presence of maternal toxicity when anidulafungin was administered to pregnant rabbits during organogenesis at 4 times the proposed therapeutic maintenance dose of 100 mg/day on the basis of relative body surface area (see Data). Inform pregnant woman of the risk to the fetus.

The estimated background risk of major birth defects and miscarriage for the indicated populations are unknown. All pregnancies have a background risk of birth defect, loss, or other adverse outcomes. In the U.S. general population, the estimated background risk of major birth defects and miscarriage in clinically recognized pregnancies is 2 to 4% and 15 to 20% respectively.

Data

Animal Data

In a combined fertility and embryo-fetal development study in rats dosed with anidulafungin for 4 weeks prior to cohabitation and through cohabitation for males or for 2 weeks prior to cohabitation and continuing through gestation day 19 for females, there was no maternal or embryo-fetal toxicity at intravenous doses up to 20 mg/kg/day (equivalent to 2 times the proposed therapeutic maintenance dose of 100 mg/day on the basis of relative body surface area).

In a rabbit embryo-fetal development study, intravenous administration of anidulafungin (0, 5, 10, and 20 mg/kg/day) from gestation day 7 through 19, resulted in reduced fetal weights and incomplete ossification in the presence of maternal toxicity (decreased body weight gain) at 20 mg/kg/day (equivalent to 4 times the proposed therapeutic maintenance dose of 100 mg/day on the basis of relative body surface area).

In a pre- and postnatal development study, pregnant rats were intravenously administered anidulafungin at doses of 2, 6, or 20 mg/kg/day from gestation day 7 through lactation day 20. Maternal toxicity was observed at ≥6 mg/kg/day (clinical signs at ≥6 mg/kg/day and reduced body weight gain and food consumption during gestation at 20 mg/kg/day group). There were no effects on the viability or growth and development of the offspring. In this study, anidulafungin was detected in fetal plasma, indicating that it crossed the placental barrier.

8.2 Lactation

Risk Summary

There are no data on the presence of anidulafungin in human milk, the effects on the breastfed infant or the effects on milk production. When a drug is present in animal milk, it is likely that the drug will be present in human milk. Anidulafungin was found in the milk of lactating rats (see Data).

The developmental and health benefits of breastfeeding should be considered along with the mother's clinical need for ERAXIS and any potential adverse effects on the breastfed child from ERAXIS or from the underlying maternal condition.

Data

Animal Data

Pregnant rats were intravenously administered anidulafungin at doses of 2, 6, or 20 mg/kg/day from gestation day 7 through lactation day 20. Milk samples were collected from 5 rats per group on lactation day 14 at approximately 1 hours post dose. Approximately dose-proportional anidulafungin concentrations were found in the milk of lactating rats.

8.4 Pediatric Use

The safety and effectiveness of ERAXIS for the treatment of candidemia and the following Candida infections: intra-abdominal abscess and peritonitis, have been established in pediatric patients 1 month of age and older. Use of ERAXIS for this indication in this age group is supported by evidence from adequate and well-controlled studies in adults with additional pharmacokinetic, safety data in pediatric patients 1 month of age and older [see Indications and Usage (1), Adverse Reactions (6.1), Clinical Pharmacology (12.3), and Clinical Studies (14.1)].

The safety and effectiveness of ERAXIS in patients younger than 1 month of age with candidemia/invasive candidiasis has not been established.

Candidemia/invasive candidiasis in pediatric patients younger than 1 month of age has a higher rate of central nervous system (CNS) and multi-organ dissemination than in older patients. In addition, in patients younger than 1 month of age ERAXIS carries a potential risk of life-threatening toxicity associated with high doses of polysorbate 80, an inactive ingredient in ERAXIS [see Warnings and Precautions (5.3)].

The safety and effectiveness of ERAXIS in pediatric patients with esophageal candidiasis has not been established.

ERAXIS is contraindicated in adult and pediatric patients with HFI. Because a diagnosis of HFI may not yet be established in pediatric patients, obtain a careful history of HFI symptoms with fructose/sucrose exposure prior to administration of ERAXIS [see Warnings and Precautions (5.4)].

8.5 Geriatric Use

Of the total number of subjects (N = 197) in the pivotal clinical studies of anidulafungin, 35% were 65 years and over, while 18% were 75 years and over. No overall differences in safety or effectiveness were observed between these subjects and younger subjects, and other reported clinical experience has not identified differences in responses between the elderly and younger patients, but greater sensitivity of some older individuals cannot be ruled out.

Dosage adjustments are not required for geriatric patients [see Clinical Pharmacology (12.3)].

8.6 Hepatic Insufficiency

No dosing adjustments are required for patients with any degree of hepatic insufficiency. Anidulafungin is not hepatically metabolized. Anidulafungin pharmacokinetics were examined in subjects with Child-Pugh class A, B or C hepatic insufficiency. Anidulafungin concentrations were not increased in subjects with any degree of hepatic insufficiency. Though a slight decrease in AUC was observed in patients with Child-Pugh C hepatic insufficiency, it was within the range of population estimates noted for healthy subjects [see Clinical Pharmacology (12.3)].

8.7 Renal Insufficiency

Dosage adjustments are not required for patients with any degree of renal insufficiency including those on hemodialysis. Anidulafungin has negligible (<1%) renal clearance. In a clinical study of subjects with mild, moderate, severe or end stage (dialysis-dependent) renal insufficiency, anidulafungin pharmacokinetics were similar to those observed in subjects with normal renal function. Anidulafungin is not dialyzable and may be administered without regard to the timing of hemodialysis [see Clinical Pharmacology (12.3)].

10 OVERDOSAGE

During clinical trials a single 400 mg dose of ERAXIS was inadvertently administered as a loading dose. No clinical adverse events were reported. In a study of 10 healthy subjects administered a loading dose of 260 mg followed by 130 mg daily; 3 of the 10 subjects experienced transient, asymptomatic transaminase elevations (≤3 × ULN) [see Warnings and Precautions (5.1)].

Anidulafungin is not dialyzable.

The maximum non-lethal dose of anidulafungin in rats was 50 mg/kg, a dose which is equivalent to 10 times the recommended daily dose for esophageal candidiasis (50 mg/day) or equivalent to 5 times the recommended daily dose for candidemia and other Candida infections (100 mg/day), based on relative body surface area comparisons.

11 DESCRIPTION

ERAXIS for Injection is a sterile, lyophilized product for intravenous (IV) infusion that contains anidulafungin. ERAXIS (anidulafungin) is a semi-synthetic lipopeptide synthesized from a fermentation product of Aspergillus nidulans. Anidulafungin is an echinocandin, a class of antifungal drugs that inhibits the synthesis of 1,3-β-D-glucan, an essential component of fungal cell walls.

ERAXIS (anidulafungin) is 1-[(4R,5R)-4,5-dihydroxy-N2-[[4"-(pentyloxy)[1,1':4',1"-terphenyl]-4-yl]carbonyl]-L-ornithine]echinocandin B. Anidulafungin is a white to off-white powder that is practically insoluble in water and slightly soluble in ethanol. In addition to the active ingredient, anidulafungin, ERAXIS for Injection contains the following inactive ingredients:

50 mg/vial – fructose (50 mg), mannitol (250 mg), polysorbate 80 (125 mg), tartaric acid (5.6 mg), and sodium hydroxide and/or hydrochloric acid for pH adjustment.

100 mg/vial – fructose (100 mg), mannitol (500 mg), polysorbate 80 (250 mg), tartaric acid (11.2 mg), and sodium hydroxide and/or hydrochloric acid for pH adjustment.

The empirical formula of anidulafungin is C58H73N7O17 and the formula weight is 1140.3.

The structural formula is:

Prior to administration, ERAXIS for Injection requires reconstitution with sterile Water for Injection and subsequent dilution with either 5% Dextrose Injection, USP or 0.9% Sodium Chloride Injection, USP (normal saline).

12 CLINICAL PHARMACOLOGY

12.1 Mechanism of Action

Anidulafungin is an anti-fungal drug [see Microbiology (12.4)].

12.3 Pharmacokinetics

General Pharmacokinetic Characteristics

The pharmacokinetics of anidulafungin following intravenous (IV) administration of ERAXIS have been characterized in healthy subjects, special populations and patients. Systemic exposures of anidulafungin are dose-proportional and have low inter-subject variability (coefficient of variation <25%) as shown in Table 5. The steady state was achieved on the first day after a loading dose (twice the daily maintenance dose) and the estimated plasma accumulation factor at steady state is approximately 2.

Table 5: Mean (%CV) Steady State Pharmacokinetic Parameters of Anidulafungin Following IV Administration of ERAXIS Once Daily for 10 Days in Healthy Adult Subjects
PK Parameter [Parameters were obtained from separate studies] | Anidulafungin IV Dosing Regimen (LD/MD, mg) [LD/MD: loading dose/maintenance dose once daily]
PK Parameter [Parameters were obtained from separate studies] | 70/35 [Data were collected on Day 7] , [Safety and efficacy of these doses has not been established] (N=6) | 200/100 (N=10) | 260/130, [See OVERDOSAGE] (N=10)
Cmax, ss [mg/L] | 3.55 (13.2) | 8.6 (16.2) | 10.9 (11.7)
AUCss [mg∙h/L] | 42.3 (14.5) | 111.8 (24.9) | 168.9 (10.8)
CL [L/h] | 0.84 (13.5) | 0.94 (24.0) | 0.78 (11.3)
t1/2 [h] | 43.2 (17.7) | 52.0 (11.7) | 50.3 (9.7)
Cmax, ss = the steady state peak concentration
AUCss = the steady state area under concentration vs. time curve
CL = clearance
t1/2 = the terminal elimination half-life

The clearance of anidulafungin is about 1 L/h and anidulafungin has a terminal elimination half-life of 40–50 hours.

Distribution

The pharmacokinetics of anidulafungin following IV administration are characterized by a short distribution half-life (0.5–1 hour) and a volume of distribution of 30–50 L that is similar to total body fluid volume. Anidulafungin is extensively bound (>99%) to human plasma proteins.

Metabolism

Hepatic metabolism of anidulafungin has not been observed. Anidulafungin is not a clinically relevant substrate, inducer, or inhibitor of cytochrome P450 (CYP450) isoenzymes. It is unlikely that anidulafungin will have clinically relevant effects on the metabolism of drugs metabolized by CYP450 isoenzymes.

Anidulafungin undergoes slow chemical degradation at physiologic temperature and pH to a ring-opened peptide that lacks antifungal activity. The in vitro degradation half-life of anidulafungin under physiologic conditions is about 24 hours. In vivo, the ring-opened product is subsequently converted to peptidic degradants and eliminated.

Excretion

In a single-dose clinical study, radiolabeled (^14C) anidulafungin was administered to healthy subjects. Approximately 30% of the administered radioactive dose was eliminated in the feces over 9 days, of which less than 10% was intact drug. Less than 1% of the administered radioactive dose was excreted in the urine. Anidulafungin concentrations fell below the lower limits of quantitation 6 days post-dose. Negligible amounts of drug-derived radioactivity were recovered in blood, urine, and feces 8 weeks post-dose.

Specific Populations

Patients with fungal infections

Population pharmacokinetic analyses from four clinical trials including 107 male and 118 female patients with fungal infections showed that the pharmacokinetic parameters of anidulafungin are not affected by age, race, or the presence of concomitant medications which are known metabolic substrates, inhibitors or inducers.

The pharmacokinetics of anidulafungin in patients with fungal infections are similar to those observed in healthy subjects. The pharmacokinetic parameters of anidulafungin estimated using population pharmacokinetic modeling following IV administration of a maintenance dose of 50 mg/day or 100 mg/day (following a loading dose) of ERAXIS are presented in Table 6.

Table 6: Mean (%CV) Steady State Pharmacokinetic Parameters of Anidulafungin Following IV Administration of ERAXIS in Patients with Fungal Infections Estimated Using Population Pharmacokinetic Modeling
PK Parameter [All the parameters were estimated by population modeling using a two-compartment model with first order elimination; AUCss, Cmax,ss and Cmin,ss (steady state trough plasma concentration) were estimated using individual PK parameters and infusion rate of 1 mg/min to administer recommended doses of 50 and 100 mg/day.] | ERAXIS IV Dosing Regimen (LD/MD, mg) [LD/MD: loading dose/daily maintenance dose.]
PK Parameter [All the parameters were estimated by population modeling using a two-compartment model with first order elimination; AUCss, Cmax,ss and Cmin,ss (steady state trough plasma concentration) were estimated using individual PK parameters and infusion rate of 1 mg/min to administer recommended doses of 50 and 100 mg/day.] | 100/50 | 200/100
Cmax, ss [mg/L] | 4.2 (22.4) | 7.2 (23.3)
Cmin, ss [mg/L] | 1.6 (42.1) | 3.3 (41.8)
AUCss [mg∙h/L] | 55.2 (32.5) | 110.3 (32.5)
CL [L/h] | 1.0 (33.5)
t1/2, β [h] [t1/2, β is the predominant elimination half-life that characterizes the majority of the concentration-time profile.] | 26.5 (28.5)

Gender

Dosage adjustments are not required based on gender. Plasma concentrations of anidulafungin in healthy men and women were similar. In multiple-dose patient studies, drug clearance was slightly faster (approximately 22%) in men.

Geriatric

Dosage adjustments are not required for geriatric patients. The population pharmacokinetic analysis showed that median clearance differed slightly between the elderly group (patients ≥65, median CL=1.07 L/h) and the non-elderly group (patients <65, median CL=1.22 L/h) and the range of clearance was similar.

Race

Dosage adjustments are not required based on race. Anidulafungin pharmacokinetics were similar among Whites, Blacks, Asians, and Hispanics.

HIV Status

Dosage adjustments are not required based on HIV status, irrespective of concomitant anti-retroviral therapy.

Hepatic Insufficiency

Anidulafungin is not hepatically metabolized. Anidulafungin pharmacokinetics were examined in subjects with Child-Pugh class A, B or C hepatic insufficiency. Anidulafungin concentrations were not increased in subjects with any degree of hepatic insufficiency. Though a slight decrease in AUC was observed in patients with Child-Pugh C hepatic insufficiency, it was within the range of population estimates noted for healthy subjects [see Use in Specific Populations (8.6)].

Renal Insufficiency

Anidulafungin has negligible renal clearance. In a clinical study of subjects with mild, moderate, severe or end stage (dialysis-dependent) renal insufficiency, anidulafungin pharmacokinetics were similar to those observed in subjects with normal renal function. Anidulafungin is not dialyzable and may be administered without regard to the timing of hemodialysis [see Use in Specific Populations (8.7)].

Pediatric

The pharmacokinetics of anidulafungin after daily doses were investigated in immunocompromised pediatric (2 through 11 years) and adolescent (12 through 17 years) patients with neutropenia. The steady state was achieved on the first day after administration of the loading dose (twice the maintenance dose), and the Cmax and AUCss increased in a dose-proportional manner. Concentrations and exposures following administration of maintenance doses of 0.75 and 1.5 mg/kg/day in this population were similar to those observed in adults following maintenance doses of 50 and 100 mg/day, respectively (as shown in Table 7).

Table 7: Mean (%CV) Steady State Pharmacokinetic Parameters of Anidulafungin Following IV Administration of ERAXIS Once Daily in Pediatric Patients
PK Parameter [Data were collected on Day 5] | ERAXIS IV Dosing Regimen (LD/MD, mg/kg) [LD/MD: loading dose/daily maintenance dose]
PK Parameter [Data were collected on Day 5] | 1.5/0.75 |  | 3.0/1.5
Age Group | 2–11 years (N = 6) | 12–17 years (N = 6) | 2–11 years (N = 6) | 12–17 years (N = 6)
Cmax, ss [mg/L] | 3.32 (50.0) | 4.35 (22.5) | 7.57 (34.2) | 6.88 (24.3)
AUCss [mg∙h/L] | 41.1 (38.4) | 56.2 (27.8) | 96.1 (39.5) | 102.9 (28.2)

The pharmacokinetics of anidulafungin were also investigated in 66 pediatric patients (1 month to <18 years) with candidemia/invasive candidiasis (ICC) in a prospective, open-label, non-comparative pediatric study following administration of ERAXIS of 3 mg/kg loading dose on Day 1 and followed by 1.5 mg/kg once daily maintenance dose [see Clinical Studies (14.1)]. Based on population pharmacokinetic analysis of combined data from adult and pediatric patients with ICC, the mean steady state exposure parameters (AUC0–24,,ss Cmin,,ss and Cmax,ss) across age groups in the overall pediatric patients (Table 8) were comparable to those in adults receiving 200 mg loading dose and 100 mg once daily maintenance dose.

Table 8: Mean (%CV) Steady State Pharmacokinetic Parameters of Anidulafungin Following IV Administration of ERAXIS in Pediatric Patients with Candidemia/Invasive Candidiasis Estimated Using Population Pharmacokinetic Modeling
PK Parameter | ERAXIS IV Dosing Regimen (3 mg/kg LD/1.5 mg/kg MD) [LD/MD: loading dose on Day 1/ once daily maintenance dose.]
Age Group | 1 month to <2 years (N = 17) | 2 to < 5 years (N = 19) | 5 to <18 years (N = 30)
Cmax, ss [mg/L] | 6.7 (28.3) | 7.1 (39.4) | 6.5 (29.2)
Cmin, ss [mg/L] | 2.0 (29) | 2.5 (44) | 2.5 (38.4)
AUCss [mg∙h/L] | 69.9 (25.3) | 82.8 (38.5) | 86.8 (35.8)

Drug Interactions

In vitro studies showed that anidulafungin is not metabolized by human cytochrome P450 or by isolated human hepatocytes and does not significantly inhibit the activities of human CYP isoforms (1A2, 2B6, 2C8, 2C9, 2C19, 2D6 and 3A) in clinically relevant concentrations. No clinically relevant drug-drug interactions were observed with drugs likely to be co-administered with anidulafungin.

Cyclosporine (CYP3A4 substrate)

In a study in which 12 healthy adult subjects received 100 mg/day maintenance dose of anidulafungin following a 200 mg loading dose (on Days 1 to 8) and in combination with 1.25 mg/kg oral cyclosporine twice daily (on Days 5 to 8), the steady state Cmax of anidulafungin was not significantly altered by cyclosporine; the steady state AUC of anidulafungin was increased by 22%. A separate in vitro study showed that anidulafungin has no effect on the metabolism of cyclosporine [see Drug Interactions (7.1)].

Voriconazole (CYP2C19, CYP2C9, CYP3A4 inhibitor and substrate)

In a study in which 17 healthy subjects received 100 mg/day maintenance dose of anidulafungin following a 200 mg loading dose, 200 mg twice daily oral voriconazole (following two 400 mg loading doses) and both in combination, the steady state Cmax and AUC of anidulafungin and voriconazole were not significantly altered by co-administration [see Drug Interactions (7.2)].

Tacrolimus (CYP3A4 substrate)

In a study in which 35 healthy subjects received a single oral dose of 5 mg tacrolimus (on Day 1), 100 mg/day maintenance dose of anidulafungin following a 200 mg loading dose (on Days 4 to 12) and both in combination (on Day 13), the steady state Cmax and AUC of anidulafungin and tacrolimus were not significantly altered by co-administration [see Drug Interactions (7.3)].

Rifampin (potent CYP450 inducer)

The pharmacokinetics of anidulafungin were examined in 27 patients that were co-administered anidulafungin and rifampin. The population pharmacokinetic analysis showed that when compared to data from patients that did not receive rifampin, the pharmacokinetics of anidulafungin were not significantly altered by co-administration with rifampin [see Drug Interactions (7.4)].

Amphotericin B liposome for injection

The pharmacokinetics of anidulafungin were examined in 27 patients that were co-administered liposomal amphotericin B. The population pharmacokinetic analysis showed that when compared to data from patients that did not receive amphotericin B, the pharmacokinetics of anidulafungin were not significantly altered by co-administration with amphotericin B [see Drug Interactions (7.5)].

12.4 Microbiology

Mechanism of Action

Anidulafungin is a semi-synthetic echinocandin with antifungal activity. Anidulafungin inhibits glucan synthase, an enzyme present in fungal, but not mammalian cells. This results in inhibition of the formation of 1,3-β-D-glucan, an essential component of the fungal cell wall.

Resistance

Echinocandin resistance is due to point mutations within the genes (FKS1 and FKS2) encoding for subunits in the glucan synthase enzyme complex. There have been reports of Candida isolates with reduced susceptibility to anidulafungin, suggesting a potential for development of drug resistance. The clinical significance of this observation is not fully understood.

Antimicrobial Activity

Anidulafungin has been shown to be active against most isolates of the following microorganisms both in vitro and in clinical infections:

Candida albicans
Candida glabrata
Candida parapsilosis
Candida tropicalis

The following in vitro data are available, but their clinical significance is unknown. At least 90 percent of the following fungi exhibit an in vitro minimum inhibitory concentration (MIC) less than or equal to the susceptible breakpoint for anidulafungin against isolates of the following Candida species. However, the effectiveness of anidulafungin in treating clinical infections due to these fungi has not been established in adequate and well-controlled clinical trials:

Candida guilliermondii
Candida krusei

Susceptibility Testing

For specific information regarding susceptibility test interpretive criteria and associated test methods and quality control standards recognized by FDA for this drug, please see: https://www.fda.gov/STIC.

13 NONCLINICAL TOXICOLOGY

13.1 Carcinogenesis, Mutagenesis, Impairment of Fertility

Long-term animal carcinogenicity studies of anidulafungin have not been conducted.

Anidulafungin was not genotoxic in the following in vitro studies: bacterial reverse mutation assays, a chromosome aberration assay with Chinese hamster ovary cells, and a forward gene mutation assay with mouse lymphoma cells. Anidulafungin was not genotoxic in mice using the in vivo micronucleus assay.

Anidulafungin produced no adverse effects on fertility in male or female rats at intravenous doses of 20 mg/kg/day (equivalent to 2 times the proposed therapeutic maintenance dose of 100 mg/day on the basis of relative body surface area).

13.2 Animal Toxicology and/or Pharmacology

In 3 month studies, liver toxicity, including single cell hepatocellular necrosis, hepatocellular hypertrophy and increased liver weights were observed in monkeys and rats at doses equivalent to 5–6 times human exposure. For both species, hepatocellular hypertrophy was still noted one month after the end of dosing.

14 CLINICAL STUDIES

14.1 Candidemia and Other Candida Infections (Intra-abdominal Abscess and Peritonitis)

Adults Candidemia and Other Candida Infections (Intra-abdominal Abscess and Peritonitis) Trial

The safety and efficacy of ERAXIS were evaluated in a Phase 3, randomized, double-blind study of patients with candidemia and/or other forms of invasive candidiasis. Patients were randomized to receive once daily IV ERAXIS (200 mg loading dose followed by 100 mg maintenance dose) or IV fluconazole (800 mg loading dose followed by 400 mg maintenance dose). Patients were stratified by APACHE II score (≤20 and >20) and the presence or absence of neutropenia. Patients with Candida endocarditis, osteomyelitis or meningitis, or those with infection due to C. krusei, were excluded from the study. Treatment was administered for at least 14 and not more than 42 days. Patients in both study arms were permitted to switch to oral fluconazole after at least 10 days of intravenous therapy, provided that they were able to tolerate oral medication, were afebrile for at least 24 hours, and the last blood cultures were negative for Candida species.

Patients who received at least one dose of study medication and who had a positive culture for Candida species from a normally sterile site before entry into the study (modified intent-to-treat [MITT] population) were included in the analysis of global response at the end of IV therapy. A successful global response required clinical cure or improvement (significant, but incomplete resolution of signs and symptoms of the Candida infection and no additional antifungal treatment), and documented or presumed microbiological eradication. Patients with an indeterminate outcome were analyzed as failures in this population.

Two hundred and fifty-six patients in the intent-to-treat (ITT) population were randomized and received at least one dose of study medication. In ERAXIS-treated patients, the age range was 16–89 years, the gender distribution was 50% male and 50% female, and the race distribution was 71% White, 20% Black/African American, 7% Hispanic, 2% other races. The median duration of IV therapy was 14 and 11 days in the ERAXIS and fluconazole arms, respectively. For those who received oral fluconazole, the median duration of oral therapy was 7 days for the ERAXIS arm and 5 days for the fluconazole arm.

Patient disposition is presented in Table 9.

Table 9: Patient Disposition and Reasons for Discontinuation in Candidemia and other Candida Infections Study
 | ERAXIS | Fluconazole
 | n (%) | n (%)
Treated patients | 131 | 125
Patients completing study through 6 week follow-up | 94 (72) | 80 (64)
DISCONTINUATIONS FROM STUDY MEDICATION
Total discontinued from study medication | 34 (26) | 48 (38)
Discontinued due to adverse events | 12 (9) | 21 (17)
Discontinued due to lack of efficacy | 11 (8) | 16 (13)

Two hundred and forty-five patients (127 ERAXIS, 118 fluconazole) met the criteria for inclusion in the MITT population. Of these, 219 patients (116 ERAXIS, 103 fluconazole) had candidemia only. Risk factors for candidemia among patients in both treatment arms in this study were: presence of a central venous catheter (78%), receipt of broad-spectrum antibiotics (69%), recent surgery (42%), recent hyperalimentation (25%), and underlying malignancy (22%). The most frequent species isolated at baseline was C. albicans (62%), followed by C. glabrata (20%), C. parapsilosis (12%) and C. tropicalis (11%). The majority (97%) of patients were non-neutropenic (ANC >500) and 81% had APACHE II scores less than or equal to 20.

Global success rates in patients with candidemia and other Candida infections are summarized in Table 10.

Table 10: Efficacy Analysis: Global Success in patients with Candidemia and other Candida Infections (MITT Population)
Time-point | ERAXIS (N=127) n (%) | Fluconazole (N=118) n (%) | Treatment Difference [Calculated as ERAXIS minus fluconazole] , % (95% C.I.)
End of IV Therapy | 96 (75.6) | 71 (60.2) | 15.4 (3.9, 27.0)
End of All Therapy [33 patients in each study arm (26% ERAXIS and 29% fluconazole-treated) switched to oral fluconazole after the end of IV therapy.] | 94 (74.0) | 67 (56.8) | 17.2 (2.9, 31.6) [98.3% confidence intervals, adjusted post hoc for multiple comparisons of secondary time points]
2 Week Follow-up | 82 (64.6) | 58 (49.2) | 15.4 (0.4, 30.4)
6 Week Follow-up | 71 (55.9) | 52 (44.1) | 11.8 (-3.4, 27.0)

Table 11 presents global response by patients with candidemia or multiple sites of Candida infection and mortality data for the MITT population.

Table 11: Global Response and Mortality in Candidemia and other Candida Infections
 | ERAXIS | Fluconazole | Between group difference [Calculated as ERAXIS minus fluconazole] (95% CI)
No. of MITT patients | 127 | 118
Global Success (MITT) At End Of IV Therapy
Candidemia | 88/116 (75.9%) | 63/103 (61.2%) | 14.7 (2.5, 26.9)
Neutropenic | 1/2 | 2/4 | -
Non neutropenic | 87/114 (76.3%) | 61/99 (61.6%) | -
Multiple sites
Peritoneal fluid/ intra-abdominal abscess | 4/6 | 5/6 | -
Blood/ peritoneum (intra-abdominal abscess) | 2/2 | 0/2 | -
Blood /bile | - | 1/1 | -
Blood/renal | - | 1/1 | -
Pancreas | - | 0/3 | -
Pelvic abscess | - | 1/2 | -
Pleural fluid | 1/1 | - | -
Blood/ pleural fluid | 0/1 | - | -
Blood/left thigh lesion biopsy | 1/1 | - | -
Total | 8/11 (72.7%) | 8/15 (53.3%) | -
Mortality
Overall study mortality | 29/127 (22.8 %) | 37/118 (31.4%) | -
Mortality during study therapy | 10/127 (7.9%) | 17/118 (14.4%) | -
Mortality attributed to Candida | 2/127 (1.6%) | 5/118 (4.2%) | -

Pediatric Candidemia/Invasive Candidiasis Trial

A prospective, open-label, non-comparative, multinational trial (National Clinical Trial (NCT) number 00761267) assessed the safety and efficacy of ERAXIS in 68 pediatric patients aged 1 month to <18 years with candidemia/invasive candidiasis. Patients were stratified by age (1 month to <2 years, 2 to <5 years, and 5 to <18 years) and received once daily intravenous ERAXIS (3 mg/kg loading dose on Day 1, and 1.5 mg/kg daily maintenance dose thereafter) followed by an optional switch to oral fluconazole (6–12 mg/kg/day, maximum 800 mg/day) up to Day 49. Patients were followed at 2 and 6 weeks after EOT.

Among 68 ERAXIS-treated patients, 64 had microbiologically confirmed Candida infection and were evaluated for efficacy in the modified intent-to-treat (MITT) population. Overall, 59 patients (92.2%) had Candida isolated from blood only. The most commonly isolated pathogens were Candida albicans (25 [39.1%] patients), followed by Candida parapsilosis (17 [26.6%] patients), and Candida tropicalis (9 [14.1%] patients). A successful global response was defined as having both successful clinical (cure or improvement) and microbiological (eradication or presumed eradication) response. The overall rates of successful global response in the MITT population are presented in Table 12 below.

Table 12: Summary of Successful Global Response by Age Group, MITT Population
 |  | Successful Global Response, n (%)
Timepoint | Global Response | 1 month to <2 years (N = 16) n (n/N, %) | 2 to <5 years (N=18) n (n/N, %) | 5 to <18 years (N=30) n (n/N, %) | Overall (N=64) n (n/N, %)
EOIVT | Success | 11 (68.8) | 14 (77.8) | 20 (66.7) | 45 (70.3)
EOIVT | 95% CI | (41.3, 89.0) | (52.4, 93.6) | (47.2, 82.7) | (57.6, 81.1)
EOT | Success | 11 (68.8) | 14 (77.8) | 21 (70.0) | 46 (71.9)
EOT | 95% CI | (41.3, 89.0) | (52.4, 93.6) | (50.6, 85.3) | (59.2, 82.4)
2-week FU | Success | 11 (68.8) | 13 (72.2) | 22 (73.3) | 46 (71.9)
2-week FU | 95% CI | (41.3, 89.0) | (46.5, 90.3) | (54.1, 87.7) | (59.2, 82.4)
6-week FU | Success | 11 (68.8) | 12 (66.7) | 20 (66.7) | 43 (67.2)
6-week FU | 95% CI | (41.3, 89.0) | (41.0, 86.7) | (47.2, 82.7) | (54.3, 78.4)
95% CI = exact 95% confidence interval for binomial proportions using Clopper-Pearson method; EOIVT = end of intravenous treatment; EOT = end of treatment; FU = follow-up; MITT = modified intent-to-treat; N = number of subjects in the population; n = number of subjects with responses.

14.2 Esophageal Candidiasis

ERAXIS was evaluated in a double-blind, double-dummy, randomized Phase 3 study. Three hundred patients received ERAXIS (100 mg loading dose IV on Day 1 followed by 50 mg/day IV) and 301 received oral fluconazole (200 mg loading dose on Day 1 followed by 100 mg/day). Treatment duration was 7 days beyond resolution of symptoms for a minimum of 14 and a maximum of 21 days.

Of the 442 patients with culture confirmed esophageal candidiasis, most patients (91%) had C. albicans isolated at the baseline.

Treatment groups were similar in demographic and other baseline characteristics. In ERAXIS-treated patients, the age range was 16–69 years, the gender distribution was 42% male and 58% female, and the race distribution was 15% White, 49% Black/African American, 15% Asian, 0.3 % Hispanic, 21% other races.

In this study, of 280 patients tested, 237 (84.6%) tested HIV positive. In both groups the median time to resolution of symptoms was 5 days and the median duration of therapy was 14 days.

Efficacy was assessed by endoscopic outcome at end of therapy (EOT). Patients were considered clinically evaluable if they received at least 10 days of therapy, had an EOT assessment with a clinical outcome other than 'indeterminate', had an endoscopy at EOT, and did not have any protocol violations prior to the EOT visit that would affect an assessment of efficacy.

An endoscopic success, defined as cure (endoscopic grade of 0 on a 4-point severity scale) or improvement (decrease of one or more grades from baseline), was seen in 225/231 (97.4%) ERAXIS-treated patients and 233/236 (98.7%) fluconazole-treated patients (Table 13). The majority of these patients were endoscopic cures (grade=0). Two weeks after completing therapy, the ERAXIS group had significantly more endoscopically-documented relapses than the fluconazole group, 120/225 (53.3%) vs. 45/233 (19.3%), respectively (Table 13).

Table 13: Endoscopy Results in Patients with Esophageal Candidiasis (Clinically Evaluable Population)
Endoscopic Response at End of Therapy
Response |  | ERAXIS N=231 | Fluconazole N=236 | Treatment Difference [Calculated as ERAXIS minus fluconazole] | 95% CI
Endoscopic Success, n (%) |  | 225 (97.4) | 233 (98.7) | -1.3% | -3.8%, 1.2%
 | Cure | 204 (88.3) | 221 (93.6)
 | Improvement | 21 (9.1) | 12 (5.1)
Failure, n (%) |  | 6 (2.6) | 3 (1.3)
Endoscopic Relapse Rates at Follow-Up, 2 Weeks Post-Treatment
 |  | ERAXIS | Fluconazole | Treatment Difference | 95% CI
Endoscopic Relapse, n/N (%) |  | 120/225 (53.3%) | 45/233 (19.3%) | 34.0% | 25.8%, 42.3%

Clinical success (cure or improvement in clinical symptoms including odynophagia/dysphagia and retrosternal pain) occurred in 229/231 (99.1%) of the ERAXIS-treated patients and 235/236 (99.6%) of the fluconazole-treated patients at the end of therapy. For patients with C. albicans, microbiological success occurred in 142/162 (87.7%) of the ERAXIS-treated group and 157/166 (94.6%) of the fluconazole-treated group at the end of therapy. For patients with Candida species other than C. albicans, success occurred in 10/12 (83.3%) of the ERAXIS-treated group and 14/16 (87.5%) of the fluconazole-treated group.

16 HOW SUPPLIED/STORAGE AND HANDLING

16.1 How Supplied

ERAXIS (anidulafungin) for Injection is supplied in a single-dose vial of sterile, lyophilized, preservative-free, white to off-white powder. ERAXIS (anidulafungin) is available in the following packaging configuration:

Single-Dose Vial of ERAXIS 50 mg

NDC 0049-0114-28

One - 50 mg vial

Single-Dose Vial of ERAXIS 100 mg

NDC 0049-0116-28

One - 100 mg vial

16.2 Storage

ERAXIS vials

ERAXIS (unreconstituted) vials should be stored in a refrigerator at 2°C – 8°C (36°F – 46°F). Do not freeze.

Excursions for 96 hours up to 25°C (77°F) are permitted, and the vial can be returned to storage at 2°C – 8°C (36°F – 46°F).

Reconstituted solution

ERAXIS reconstituted solution can be stored at up to 25°C (77°F) for up to 24 hours [see Dosage and Administration (2.3)].

Infusion Solution

ERAXIS infusion solution can be stored at temperatures up to 25°C (77°F) for up to 48 hours. Do not freeze [see Dosage and Administration (2.4)].

17 PATIENT COUNSELING INFORMATION

Hepatic Adverse Reactions

Inform patients about the risk of developing abnormal liver function tests and/or hepatic dysfunction. Advise the patient that liver function tests may be monitored during treatment.

Anaphylactic and Hypersensitivity Reactions

Inform the patient that anaphylactic reactions, including shock were reported with ERAXIS. Inform the patient if these reactions occur, ERAXIS may be discontinued and appropriate treatment administered.

Inform the patient that ERAXIS is also known to cause infusion-related adverse reactions, possibly histamine-mediated. Inform the patient to report symptoms including rash, urticaria, flushing, pruritus, dyspnea, and hypotension to their healthcare provider.

Embryo-Fetal Toxicity

Advise pregnant women and females of reproductive potential of the potential risk of ERAXIS to a fetus. Advise females to inform their healthcare provider of a known or suspected pregnancy.

Patients with Hereditary Fructose Intolerance (HFI)

Inform patients and caregivers that ERAXIS contains fructose and can be life-threatening when administered to patients with hereditary fructose intolerance (HFI) [see Warnings and Precautions (5.4)]. Inquire for symptoms of fructose and/or sucrose intolerance.

This product's prescribing information may have been updated. For current full prescribing information, please visit www.pfizer.com.

For medical information about ERAXIS, please visit www.pfizermedinfo.com or call 1-800-438-1985.

LAB-0336-16.0

PRINCIPAL DISPLAY PANEL - 50 mg Vial Label

1 Sterile Single-dose Vial

Eraxis®
(anidulafungin)
for Injection

50 mg/vial

For Intravenous Infusion Only

Pfizer
Hospital

Distributed by
Roerig
Division of Pfizer Inc.
New York, NY 10001

Rx only

PRINCIPAL DISPLAY PANEL - 50 mg Vial Carton

NDC 0049-0114-28

Unit Pack Contains:
1 Sterile Single-dose Vial
Eraxis® 50 mg

Eraxis®
(anidulafungin)
for Injection

50 mg/vial

For Intravenous Infusion Only

Store Vial in Refrigerator
at 2° C - 8° C (36° F - 46° F).
Do Not Freeze.

Pfizer
Hospital

Distributed by
Roerig
Division of Pfizer Inc.
New York, NY 10001

Rx only

PRINCIPAL DISPLAY PANEL - 100 mg Vial Label

1 Sterile Single-dose Vial

Eraxis®
(anidulafungin)
for Injection

100 mg/vial

For Intravenous Infusion Only

Pfizer
Hospital

Distributed by
Roerig
Division of Pfizer Inc.
New York, NY 10001

Rx only

PRINCIPAL DISPLAY PANEL - 100 mg Vial Carton

NDC 0049-0116-28

Unit Pack Contains:
1 Sterile Single-dose Vial
Eraxis® 100 mg

Eraxis®
(anidulafungin)
for Injection

100 mg/vial

For Intravenous Infusion Only

Store Vial in Refrigerator
at 2° C - 8° C (36° F - 46° F).
Do Not Freeze.

Pfizer
Hospital

Distributed by
Roerig
Division of Pfizer Inc.
New York, NY 10001

Rx only